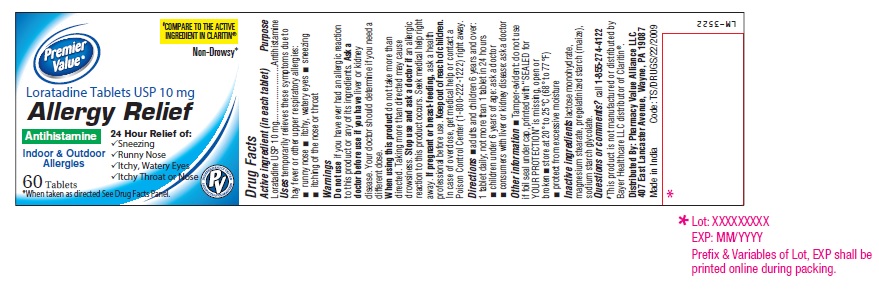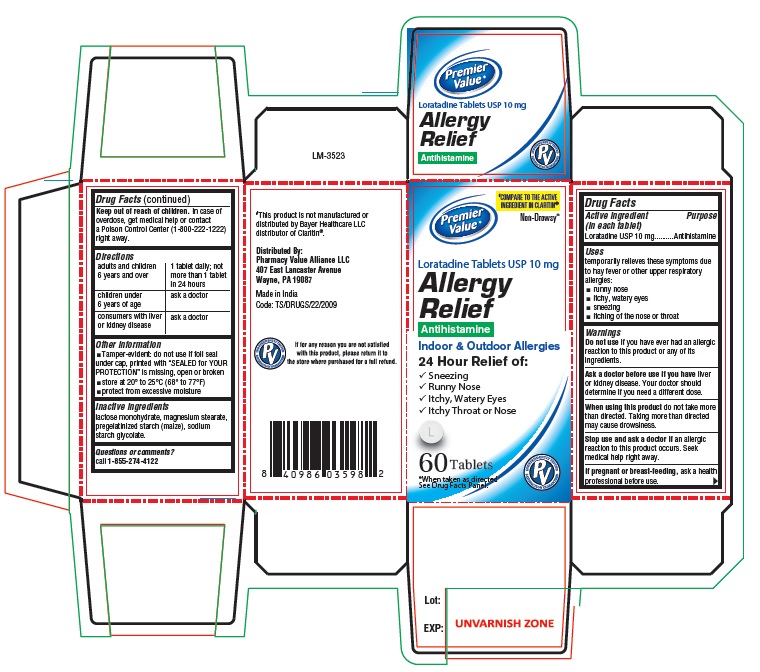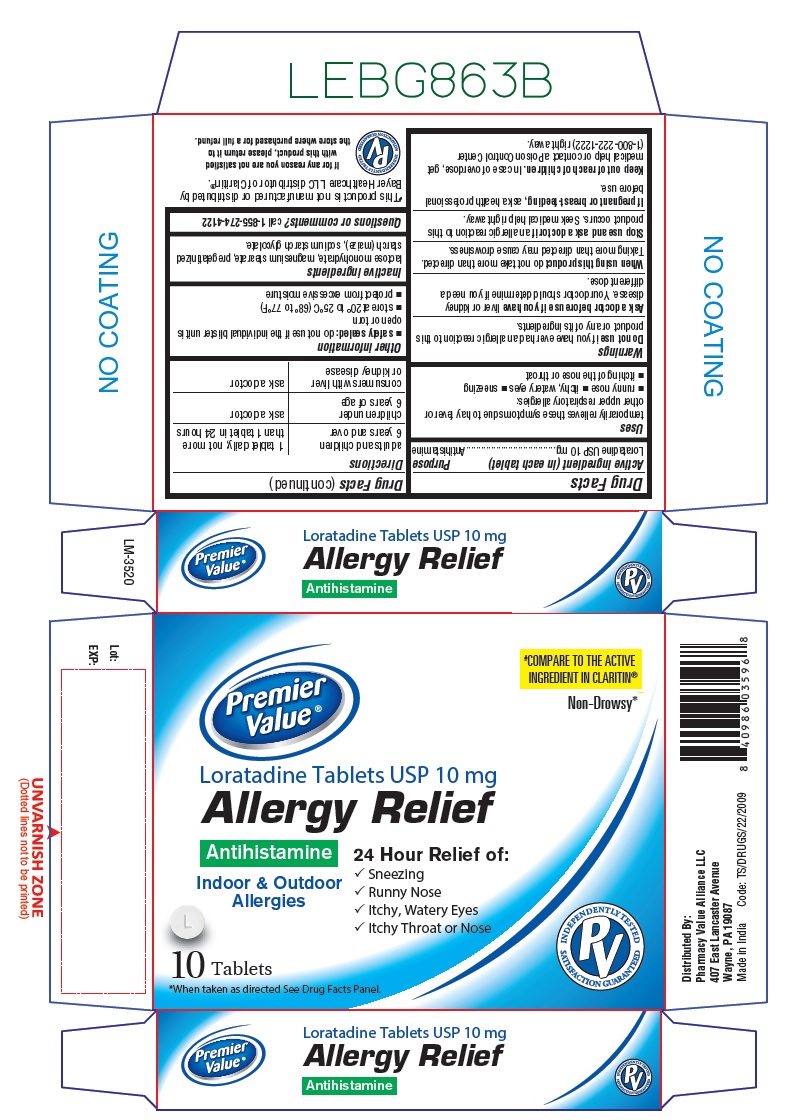 DRUG LABEL: Loratadine
NDC: 68016-094 | Form: TABLET
Manufacturer: Chain Drug Consortium, LLC
Category: otc | Type: Human OTC Drug Label
Date: 20221104

ACTIVE INGREDIENTS: LORATADINE 10 mg/1 1
INACTIVE INGREDIENTS: LACTOSE MONOHYDRATE; MAGNESIUM STEARATE; STARCH, CORN; SODIUM STARCH GLYCOLATE TYPE A POTATO

Loratadine Tablets USP 10 mg

Active ingredient (in each tablet)

Loratadine USP 10 mg

Purpose

Antihistamine

Uses

temporarily relieves these symptoms due to hay fever or other upper respiratory allergies:

- runny nose
- itchy, watery eyes
- sneezing
- itching of the nose or throat

Warnings

Do not use
if you have ever had an allergic reaction to this product or any of its ingredients.

Ask a doctor before use if you have

liver or kidney disease. Your doctor should determine if you need a different dose.

When using this product

do not take more than directed. Taking more than directed may cause drowsiness.

Stop use and ask a doctor if

an allergic reaction to this product occurs. Seek medical help right away.

If pregnant or breast-feeding,

ask a health professional before use.

Keep out of reach of children.

In case of overdose, get medical help or contact a Poison Control Center (1-800-222-1222) right away.

Directions

adults and children 6 years and over | 1 tablet daily; not more than 1 tablet in 24 hours
children under 6 years of age | ask a doctor
consumers with liver or kidney disease | ask a doctor

Other information

- Tamper-evident: do not use if foil seal under cap, printed with “SEALED for YOUR PROTECTION” is missing, open or broken
- store at 20° to 25°C (68° to 77°F)
- protect from excessive moisture

Inactive ingredients

lactose monohydrate, magnesium stearate, pregelatinized starch (maize), sodium starch glycolate.

Questions or comments?

call 1-855-274-4122
#This product is not manufactured or distributed by Bayer Healthcare LLC distributor of Claritin®.
Distributed By:
Pharmacy Value Alliance LLC
407 East Lancaster Avenue,
Wayne, PA 19087
Made in India
Code: TS/DRUGS/22/2009

PACKAGE LABEL-PRINCIPAL DISPLAY PANEL - 10 mg (60 Tablets Bottle)

#COMPARE TO THE ACTIVE
INGREDIENT IN CLARITIN®
Non-Drowsy*
Premier
Value®
Loratadine Tablets USP 10 mg
Allergy Relief
Antihistamine

Indoor & Outdoor
Allergies
24 Hour Relief of:
• Sneezing
• Runny Nose
• Itchy, Watery Eyes
• Itchy Throat or Nose
60 Tablets
*When taken as directed See Drug Facts Panel.

PACKAGE LABEL-PRINCIPAL DISPLAY PANEL - 10 mg Container Carton (60 Tablets)

#COMPARE TO THE ACTIVE
INGREDIENT IN CLARITIN®
Non-Drowsy*
Premier
Value®
Loratadine Tablets USP 10 mg
Allergy
Relief
Antihistamine
Indoor & Outdoor Allergies
24 Hours Relief of:
• Sneezing
• Runny Nose
• Itchy, Watery Eyes
• Itchy Throat or Nose
60 Tablets
*When taken as directed
See Drug Facts Panel.

PACKAGE LABEL-PRINCIPAL DISPLAY PANEL - 10 mg Blister Carton (30 Tablets)

#COMPARE TO THE ACTIVE
INGREDIENT IN CLARITIN®
Non-Drowsy*
Premier
Value®
Loratadine Tablets USP 10 mg
Allergy Relief
Antihistamine
Indoor & Outdoor
Allergies
24 Hours Relief of:
• Sneezing
• Runny Nose
• Itchy, Watery Eyes
• Itchy Throat or Nose
10 Tablets
*When taken as directed See Drug Facts Panel.